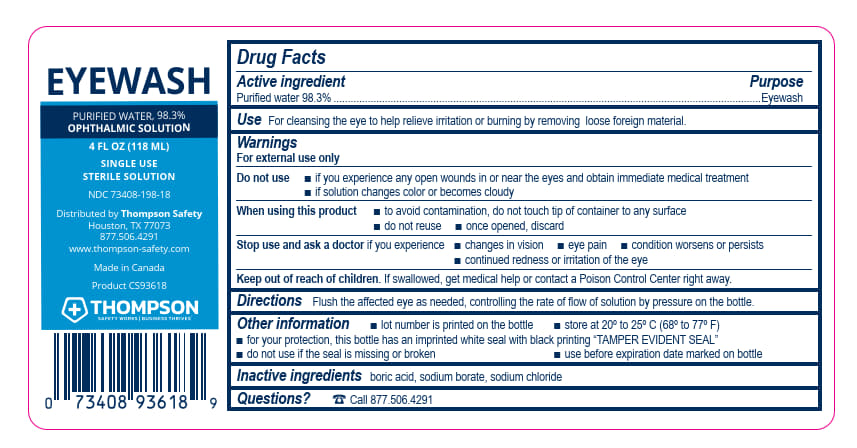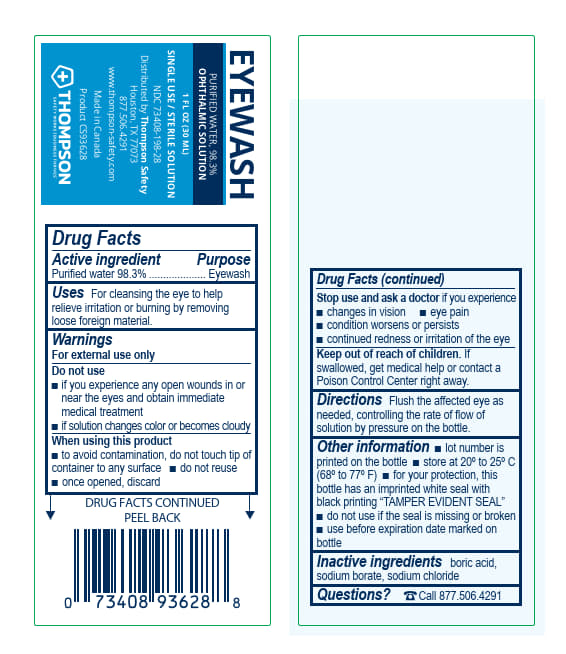 DRUG LABEL: Thompson Safety Eyewash
NDC: 73408-198 | Form: SOLUTION
Manufacturer: Thompson Safety
Category: otc | Type: HUMAN OTC DRUG LABEL
Date: 20240712

ACTIVE INGREDIENTS: WATER 929 g/946 mL
INACTIVE INGREDIENTS: BORIC ACID; SODIUM CHLORIDE; SODIUM BORATE

Thompson Safety Eyewash

Drug Facts

Active Ingredient

Purified water 98.3%

Purpose

Eye wash

Uses

For cleansing the eye to remove loose foreign material and to also releive irritation and burning.

Warnings

For external use only

Do not use

if you experience any open wounds in or near the eyes and get medical help right away
if solution changes color or becomes cloudy

When using this product

to avoid contamination, do not touch tip of container to any surface
do not reuse
once opened, discard

Stop use and ask a doctor if

you experience

eye pain
changes in vision
continued redness or irritation of the eye
condition worsens or persists

Keep out of reach of children.

Directions

Flush the affected eye as needed, controlling the rate of flow of solution by pressure on the bottle.

Other information

for your protection, this bottle has an imprinted white seal with black printing “TAMPER EVIDENT SEAL”
do not use if this seal is missing or broken
use before expiration date marked on bottle
lot number is printed on the bottle
store at 20º to 25º C [68º to 77º F]

Inactive ingredients

boric acid, sodium borate, sodium chloride

Thompson Safety Eyewash 1 oz

EYEWASH

PURIFIED WATER, 98.3%

OPHTHALMIC SOLUTION

1 FL OZ (30 ML)

SINGLE USE / STERILE SOLUTION

NDC 73408-198-28

Distributed by Thompson Safety

Houston, TX 77073

877.506.4291

www.thompson-safety.com

Made in Canada

Product CS93628

THOMPSON

SAFETY WORKS BUSINESS THRIVES™

Thompson Safety Eyewash 4 oz

EYEWASH

PURIFIED WATER, 98.3%

OPHTHALMIC SOLUTION

4 FL OZ (118 ML)

SINGLE USE

STERILE SOLUTION

NDC 73408-198-28

Distributed by Thompson Safety

Houston, TX 77073

877.506.4291

www.thompson-safety.com

Made in Canada

Product CS93628

THOMPSON

SAFETY WORKS BUSINESS THRIVES™